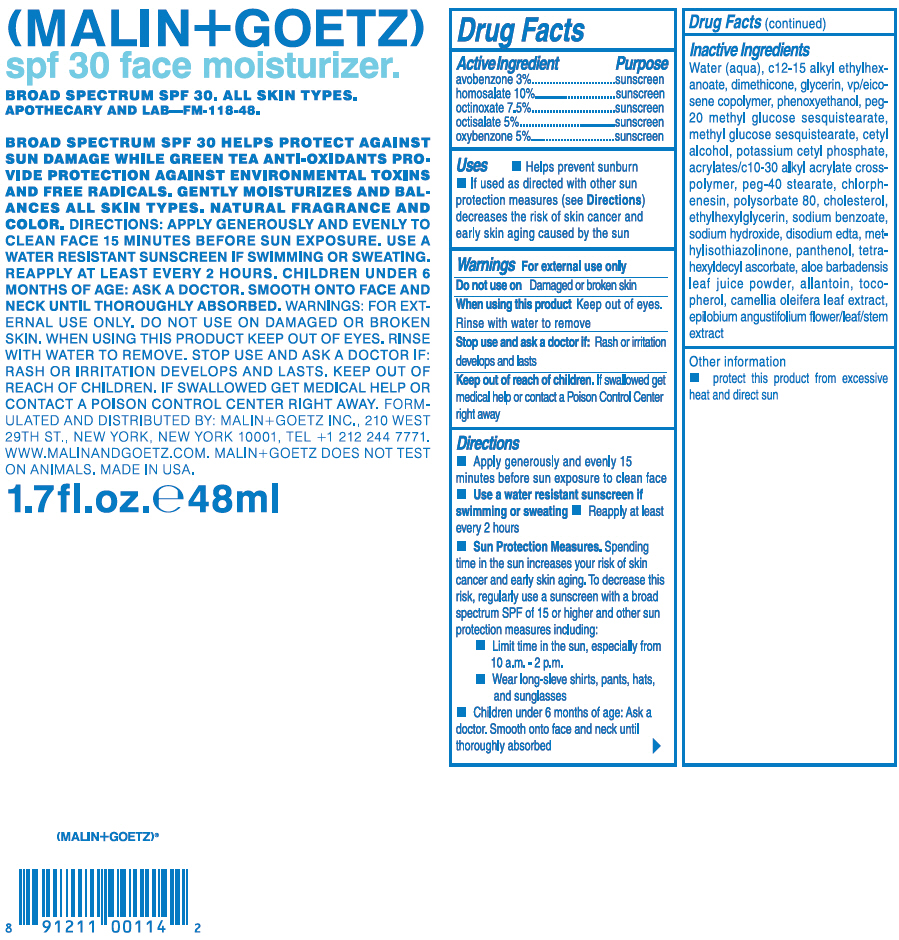 DRUG LABEL: Malin and Goetz 
NDC: 53634-254 | Form: CREAM
Manufacturer: Malin + Goetz
Category: otc | Type: HUMAN OTC DRUG LABEL
Date: 20140813

ACTIVE INGREDIENTS: avobenzone 30 mg/1 mL; homosalate 100 mg/1 mL; octinoxate 75 mg/1 mL; octisalate 50 mg/1 mL; oxybenzone 50 mg/1 mL
INACTIVE INGREDIENTS: Water; c12-15 alkyl ethylhexanoate; dimethicone; glycerin; phenoxyethanol; peg-20 methyl glucose sesquistearate; cetyl alcohol; potassium cetyl phosphate; peg-40 stearate; chlorphenesin; polysorbate 80; cholesterol; ethylhexylglycerin; sodium benzoate; sodium hydroxide; edetate disodium; methylisothiazolinone; panthenol; tetrahexyldecyl ascorbate; aloe vera leaf; allantoin; tocopherol; camellia oleifera leaf; epilobium angustifolium flowering top

Malin and Goetz
SPF 30 Face Moisturizer

Drug Facts

ACTIVE INGREDIENT

Active Ingredient | Purpose
avobenzone 3% | sunscreen
homosalate 10% | sunscreen
octinoxate 7.5% | sunscreen
octisalate 5% | sunscreen
oxybenzone 5% | sunscreen

Uses

- Helps prevent sunburn
- If used as directed with other sun protection measures (see Directions) decreases the risk of skin cancer and early skin aging caused by the sun

Warnings

For external use only

Do not use on damaged or broken skin

When using this product keep out of eyes. Rinse with water to remove

Stop use and ask a doctor if: Rash or irritation develops and lasts

Keep out of reach of children. If swallowed get medical help or contact a Poison Control Center right away

Directions

- Apply generously and evenly 15 minutes before sun exposure to clean face
- Use a water resistant sunscreen if swimming or sweating
- Reapply at least every 2 hours
- Sun Protection Measures. Spending time in the sun increases your risk of skin cancer and early skin aging. To decrease this risk, regularly use a sunscreen with a broad spectrum SPF of 15 or higher and other sun protection measures including:
  - Limit time in the sun, especially from 10 a.m. - 2 p.m.
  - Wear long-sleeve shirts, pants, hats, and sunglasses
- Children under 6 months of age: Ask a doctor. Smooth onto face and neck until thoroughly absorbed

Inactive Ingredients

Water (aqua), c12-15 alkyl ethylhexanoate, dimethicone, glycerin, vp/eicosene copolymer, phenoxyethanol, peg-20 methyl glucose sesquistearate, methyl glucose sesquistearate, cetyl alcohol, potassium cetyl phosphate, acrylates/c10-30 alkyl acrylate cross- polymer, peg-40 stearate, chlorph- enesin, polysorbate 80, cholesterol, ethylhexylglycerin, sodium benzoate, sodium hydroxide, disodium edta, methylisothiazolinone, panthenol, tetrahexyldecyl ascorbate, aloe barbadensis leaf juice powder, allantoin, tocopherol, camellia oleifera leaf extract, epilobium angustifolium flower/leaf/stem extract

Other information

- protect this product from excessive heat and direct sun

Questions or comments?

Visit www.malinandgoetz.com or call +1-212-244-7771, M-F, 9am-6pm EST

DISTRIBUTED BY:
MALIN+GOETZ INC.,
210 WEST 29TH ST.,
NEW YORK, NEW YORK 10001

PRINCIPAL DISPLAY PANEL - 48 mL Tube Carton

(MALIN+GOETZ)
spf 30 face moisturizer.

BROAD SPECTRUM SPF 30. ALL SKIN TYPES.
APOTHECARY AND LAB—FM-118-48.

BROAD SPECTRUM SPF 30 HELPS PROTECT AGAINST
SUN DAMAGE WHILE GREEN TEA ANTIOXIDANTS PRO-
VIDE PROTECTION AGAINST ENVIRONMENTAL TOXINS
AND FREE RADICALS. GENTLY MOISTURIZES AND BAL-
ANCES ALL SKIN TYPES. NATURAL FRAGRANCE AND
COLOR. DIRECTIONS: APPLY GENEROUSLY AND EVENLY TO
CLEAN FACE 15 MINUTES BEFORE SUN EXPOSURE. USE A
WATER RESISTANT SUNSCREEN IF SWIMMING OR SWEATING.
REAPPLY AT LEAST EVERY 2 HOURS. CHILDREN UNDER 6
MONTHS OF AGE: ASK A DOCTOR. SMOOTH ONTO FACE AND
NECK UNTIL THOROUGHLY ABSORBED. WARNINGS: FOR EXT-
ERNAL USE ONLY. DO NOT USE ON DAMAGED OR BROKEN
SKIN. WHEN USING THIS PRODUCT KEEP OUT OF EYES. RINSE
WITH WATER TO REMOVE. STOP USE AND ASK A DOCTOR IF:
RASH OR IRRITATION DEVELOPS AND LASTS. KEEP OUT OF
REACH OF CHILDREN. IF SWALLOWED GET MEDICAL HELP OR
CONTACT A POISON CONTROL CENTER RIGHT AWAY. FORM-
ULATED AND DISTRIBUTED BY: MALIN+GOETZ INC., 210 WEST
29TH ST., NEW YORK, NEW YORK 10001, TEL +1 212 244 7771.
WWW.MALINANDGOETZ.COM. MALIN+GOETZ DOES NOT TEST
ON ANIMALS. MADE IN USA.

1.7fl.oz.℮48ml